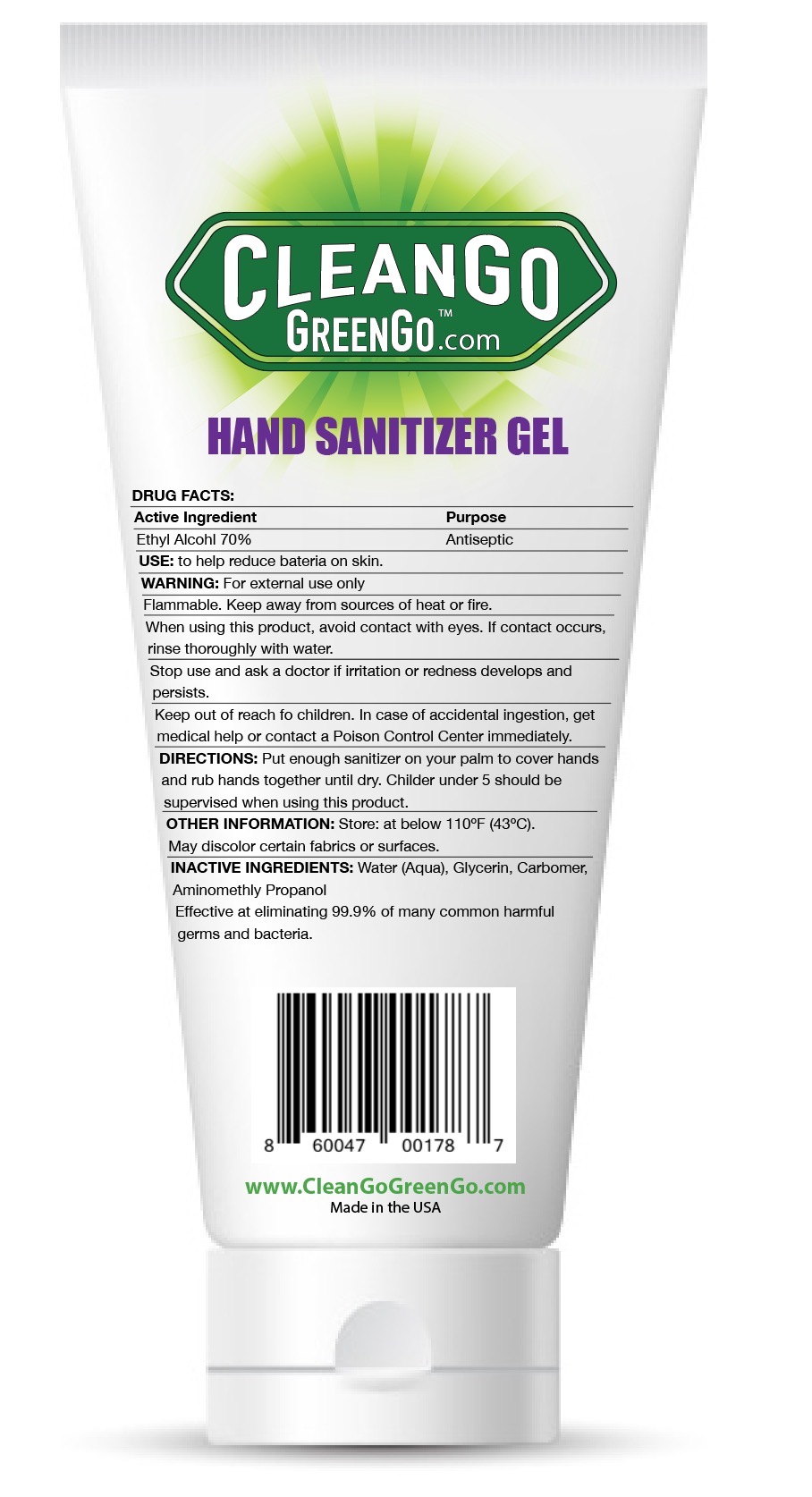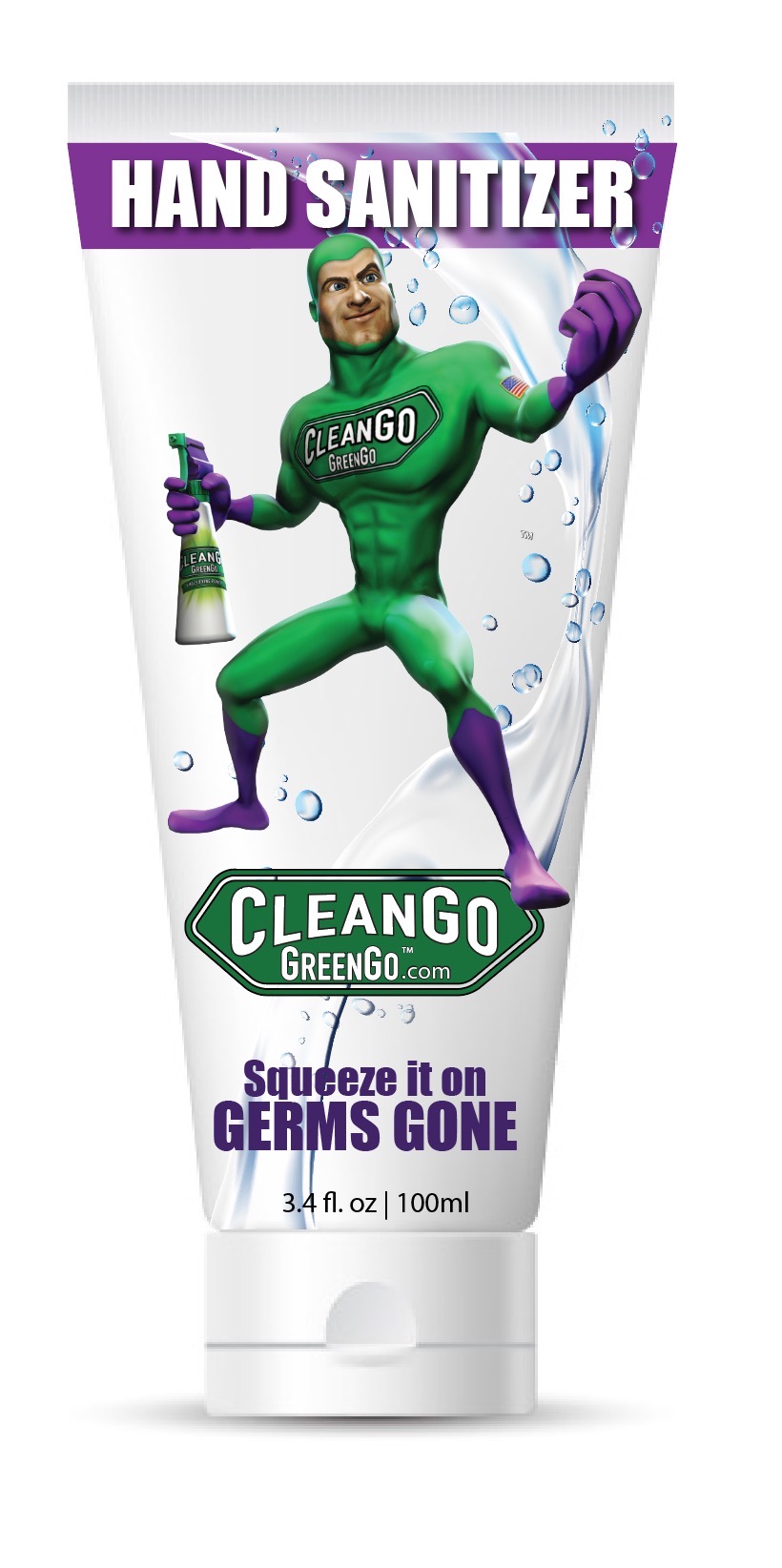 DRUG LABEL: CLEANGO GREENGO HAND SANITIZER
NDC: 76997-101 | Form: GEL
Manufacturer: CleanGo GreenGo Inc.
Category: otc | Type: HUMAN OTC DRUG LABEL
Date: 20200429

ACTIVE INGREDIENTS: ALCOHOL 70 mL/100 mL
INACTIVE INGREDIENTS: WATER; GLYCERIN; CARBOMER HOMOPOLYMER, UNSPECIFIED TYPE; AMINOMETHYLPROPANOL

CLEANGO GREENGO HAND SANITIZER

ACTIVE INGREDIENT

ETHYL ALCOHOL 70%

PURPOSE

ANTISEPTIC

USES

TO HELP REDUCE BACTERIA ON SKIN.

WARNINGS

FOR EXTERNAL USE ONLY.

FLAMMABLE. KEEP AWAY FROM SOURCES OF HEAT OR FIRE.

WHEN USING THIS PRODUCCT AVOID CONTACT WITH EYES. IF CONTACT OCCURS, RINSE THOROUGHLY WITH WATER.

STOP USE AND ASK THE DOCTOR IF IRRITATION OR REDNESS DEVELOPS AND PERSISTS.

KEEP OUT OF REACH OF CHILDREN. IN CASE OF ACCIDENTAL INGESTION, GET MEDICAL HELP OR CONTACT A POISON CONTROL CENTER IMMEDIATELY.

DIRECTIONS

- PUT ENOUGH HAND SANITIZER IN YOUR PALM TO COVER HANDS AND RUB TOGETHER UNTIL DRY.
- CHILDREN UNDER 5 YEARS SHOULD BE SUPERVISED WHEN USING THIS PRODUCT.

INACTIVE INGREDIENTS

WATER (AQUA), GLYCERIN, CARBOMER, AMINOMETHYL PROPANOL.

OTHER INFORMATION

STORE AT THE TEMPERATURE BELOW 110°F (43°C). MAY DISCOLOR CERTAIN FABRICS OR SURFACES.